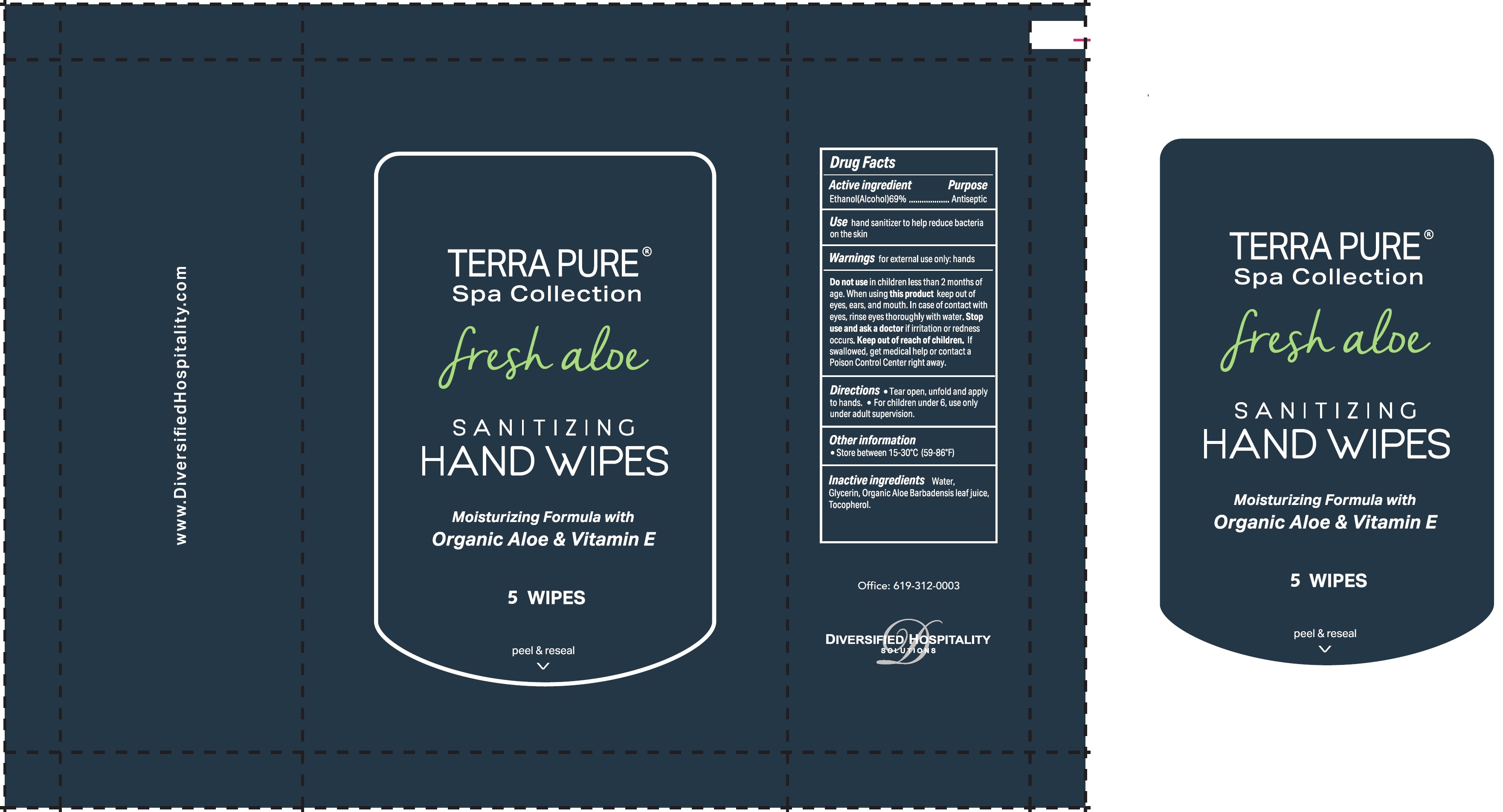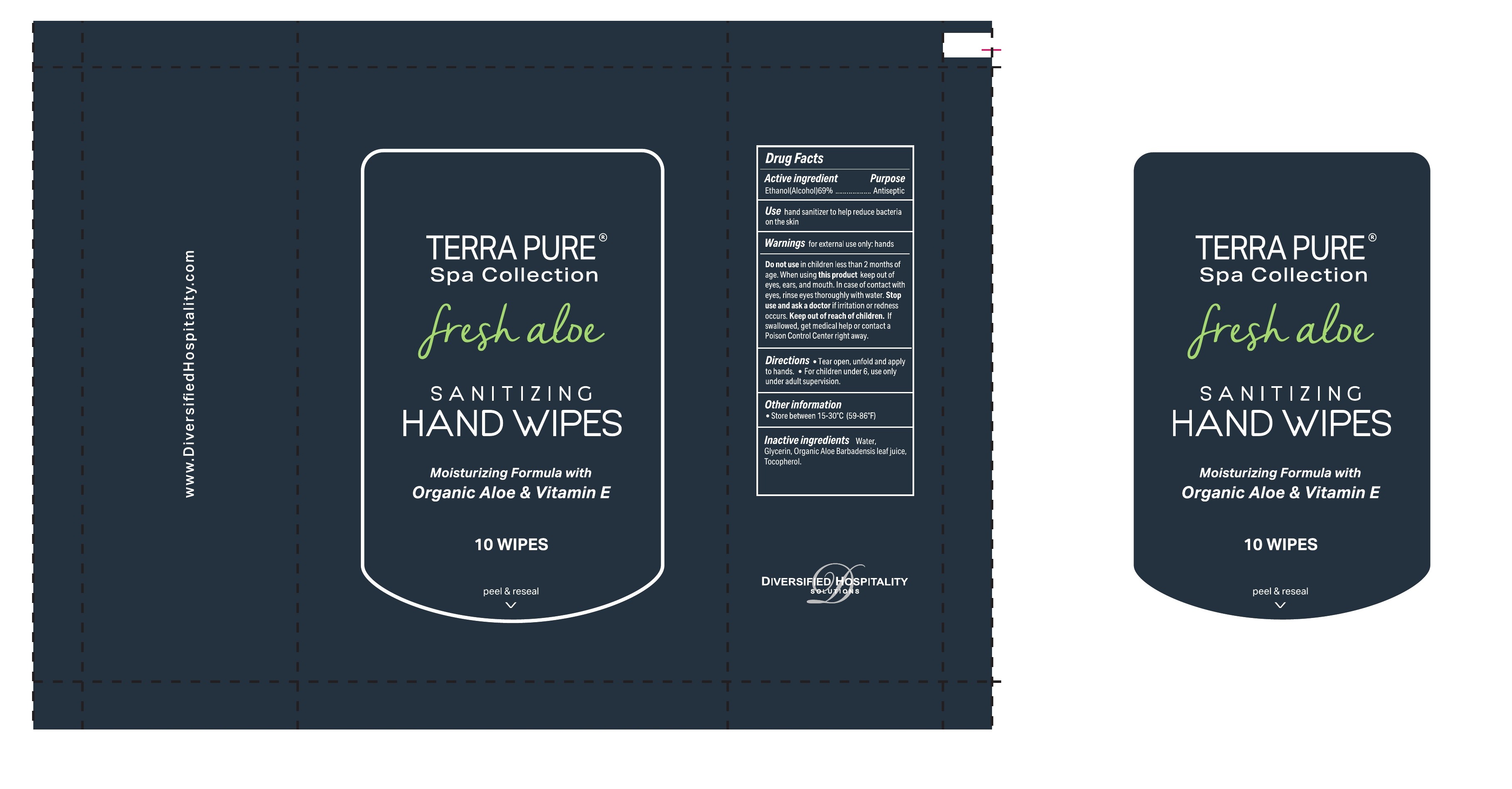 DRUG LABEL: Terra Pure Sanitizing Hand wipes
NDC: 77849-010 | Form: CLOTH
Manufacturer: Yangzhou Eco-Amenities CO., Ltd
Category: otc | Type: HUMAN OTC DRUG LABEL
Date: 20210119

ACTIVE INGREDIENTS: ALCOHOL 69 mL/1000 mL
INACTIVE INGREDIENTS: WATER; GLYCERIN; ALOE VERA LEAF; TOCOPHEROL

Terra Pure Sanitizing Hand wipes

Active ingredient

Ethanol(Alcohol)69%

Purpose

Antiseptic

Use

hand sanitizer to help reduce bacteria on the skin

Warnings

for external use only: hands

Do not use

in children less than 2 months of age.

When using this product

keep out of eyes, ears, and mouth. In case of contact with eyes, rinse eyes thoroughly with water.

Stop use and ask a doctor

if irritation and redness occurs.

Keep out of reach of children.

If swallowed, get medical help or contact a Poison Control Center right away.

Directions

- Tear open, unfold and apply to hands.
- For children under 6, use only under adult supervision.

Other information

- Store between 15-30°C (59-86°F)

Inactive ingredients

Water, Glycerin, Organic Aloe Barbadensis leaf juice, Tocopherol.